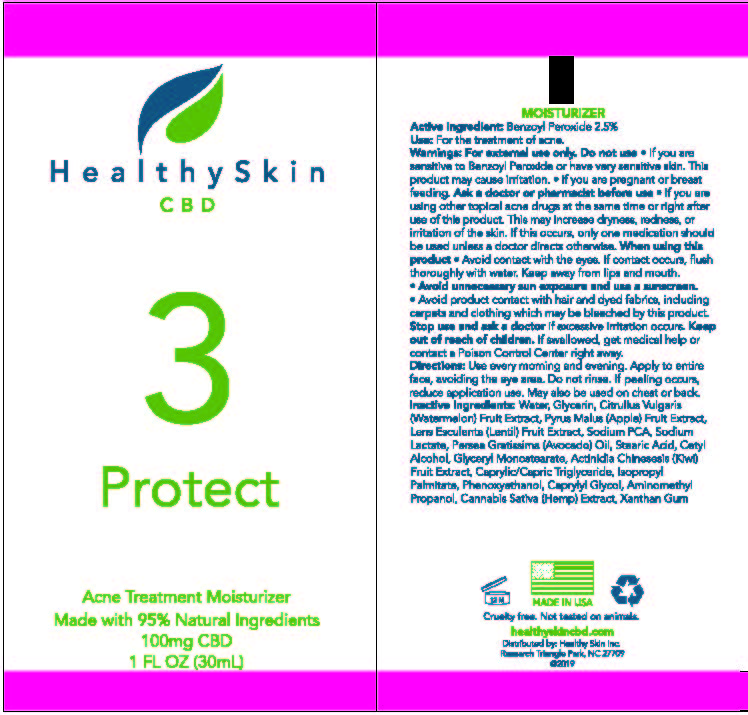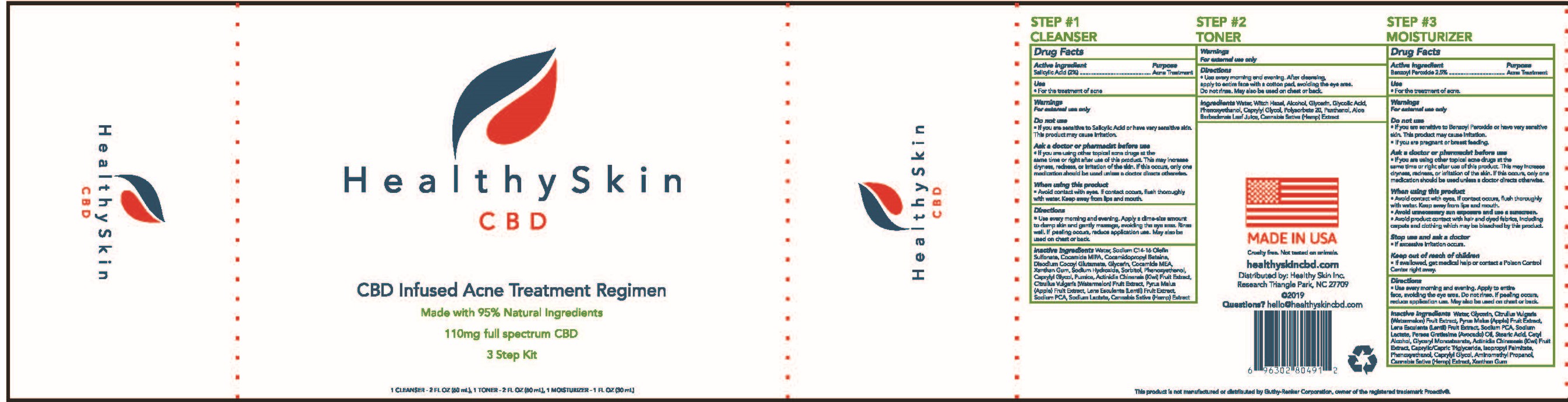 DRUG LABEL: Healthy Skin Moisturizer
NDC: 52261-3801 | Form: LOTION
Manufacturer: Cosco International, Inc.
Category: otc | Type: HUMAN OTC DRUG LABEL
Date: 20200326

ACTIVE INGREDIENTS: BENZOYL PEROXIDE 0.0625 kg/1 kg
INACTIVE INGREDIENTS: ISOPROPYL PALMITATE; XANTHAN GUM; CETYL ALCOHOL; GLYCERYL MONOSTEARATE; AVOCADO OIL; MEDIUM-CHAIN TRIGLYCERIDES; .ALPHA.-TOCOPHEROL ACETATE, DL-; GLYCERIN; STEARIC ACID; PHENOXYETHANOL; CAPRYLYL GLYCOL; WATER; WATERMELON; APPLE; LENS CULINARIS FRUIT; SODIUM LACTATE; SODIUM PYRROLIDONE CARBOXYLATE; AMINOMETHYLPROPANOL; CANNABIS SATIVA SEED OIL; KIWI FRUIT; ETHYLHEXYLGLYCERIN; SORBIC ACID

Healthy Skin Moisturizer

Drug Facts

Active Ingredient Purpose

Benzoyl Peroxide 2.5%.........Acne Treatment

Use

- For the treatment of acne.

Warnings

For external use only

Do not use

- If you are sensitive to Benzoyl Peroxide or have very sensitive skin. This product may cause irritation.
- If you are pregnant or breast feeding.

Ask a doctor or pharmacist before use

- If you are using other topical ance drugs at the same time or right after use of this product. This may increase dryness, redness, or irritation of the skin. If this occurs, only one medication should be used unless a doctor directs otherwise.

When using this product

- Avoid contact with eyes. If contact occurs, flush thoroughly with water. Keep away from lips and mouth.
- Avoid unneccesary sun exposure and use a sunscreen.
- Avoid product contact with hair and dyed fabrics, including carpets and clothing which may be bleached by this product.

Stop use and ask a doctor

- If excessive irritation occurs.

Keep out of reach of children

- If swallowed, get medical help or contact a Poison Control Center right away.

Directions

- Use every morning and evening. Apply to entire face, avoiding the eye area. Do not rinse. If peeling occurs, reduce application use. May also be used on chest and back.

INACTIVE INGREDIENT

Inactive Ingredients .Alpha.Tocopherol, DL-, Actinidia Chinensis (Kiwi) Fruit Extract, Aminomethylproanol, Cannabis Sativa Seed Oil, Caprylyl Glycol, Cetyl Alcohol, Citrullus Lanatis (Watermelon) Fruit Extract, Ethylhexylglycerin, Glycerin, Glyceryl Monostearate, Isopropyl Palmitate, Lens Esculenta (Lentil) Fruit Extract, Medium-Chain Triglycerides, Persea Gratissima (Avocado) Oil, Phenoxyethanol, Pyrus Malus (Apple) Fruit Extract, Sodium Lactate, Sodium Pyrrolidone Carboxylate, Sorbic Acid, Stearic Acid, Water, Xanthan Gum

Questions? Hello@healthyskincbd.com